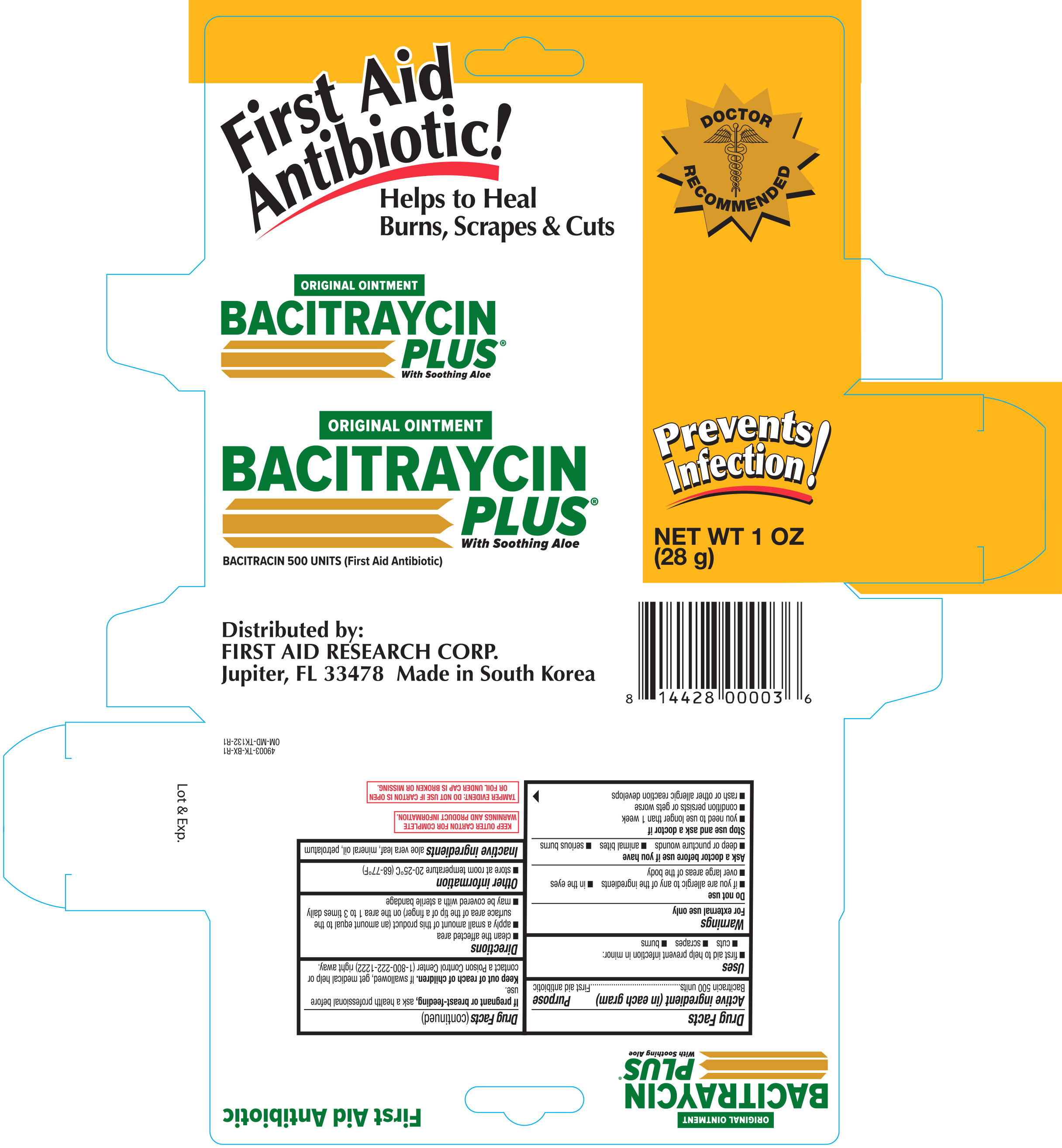 DRUG LABEL: First Aid Antibiotic Bacitraycin Plus
NDC: 75983-000 | Form: CREAM
Manufacturer: First Aid Research Corp.
Category: otc | Type: HUMAN OTC DRUG LABEL
Date: 20190711

ACTIVE INGREDIENTS: BACITRACIN 500 [USP'U]/1 g
INACTIVE INGREDIENTS: ALOE VERA LEAF; LIGHT MINERAL OIL; PETROLATUM

First Aid Original Bacitraycin Plus Ointment 1 oz 49003 (2019)

Active ingredient (each gram contains) Purpose

Bacitracin 500 units.........................................................................................First Aid Antibiotic

PURPOSE

Uses first aid to help prevent infection in

- minor cuts
- scrapes
- burns

Warnings For external use only.

Do not use

- in the eyes
- over large areas of the body
- if you are allergic to any of the ingredients
- longer than 1 week unless directed by a doctor

Ask a doctor before use in case of deep or puncture wounds, animal bites, or serious burns.

Stop use and ask a doctor if

- you need to use longer than 1 week
- condition persists or gets worse
- rash or other allergic reaction develops

PREGNANCY OR BREAST FEEDING

If pregnant or breast-feeding, ask a health professional before use.

Keep out of reach of children. If swallowed, get medical help or contact a Poison Control Center (1-800-222-1222) right away.

Directions

- clean the affected area
- apply a small amount of this product (an amount equal to the surface area of the tip of a finger) on the area 1 to 3 times daily
- may be covered with a sterile bandage

Other information

- store at 20° to 25° C (68° to 77° F)

INACTIVE INGREDIENT

Inactive ingredients aloe vera gel, light mineral oil and petrolatum

DOSAGE AND ADMINISTRATION

Distributed by:

First Aid Research Corp.

Jupiter, FL 33478 U.S.A.

Made in South Korea